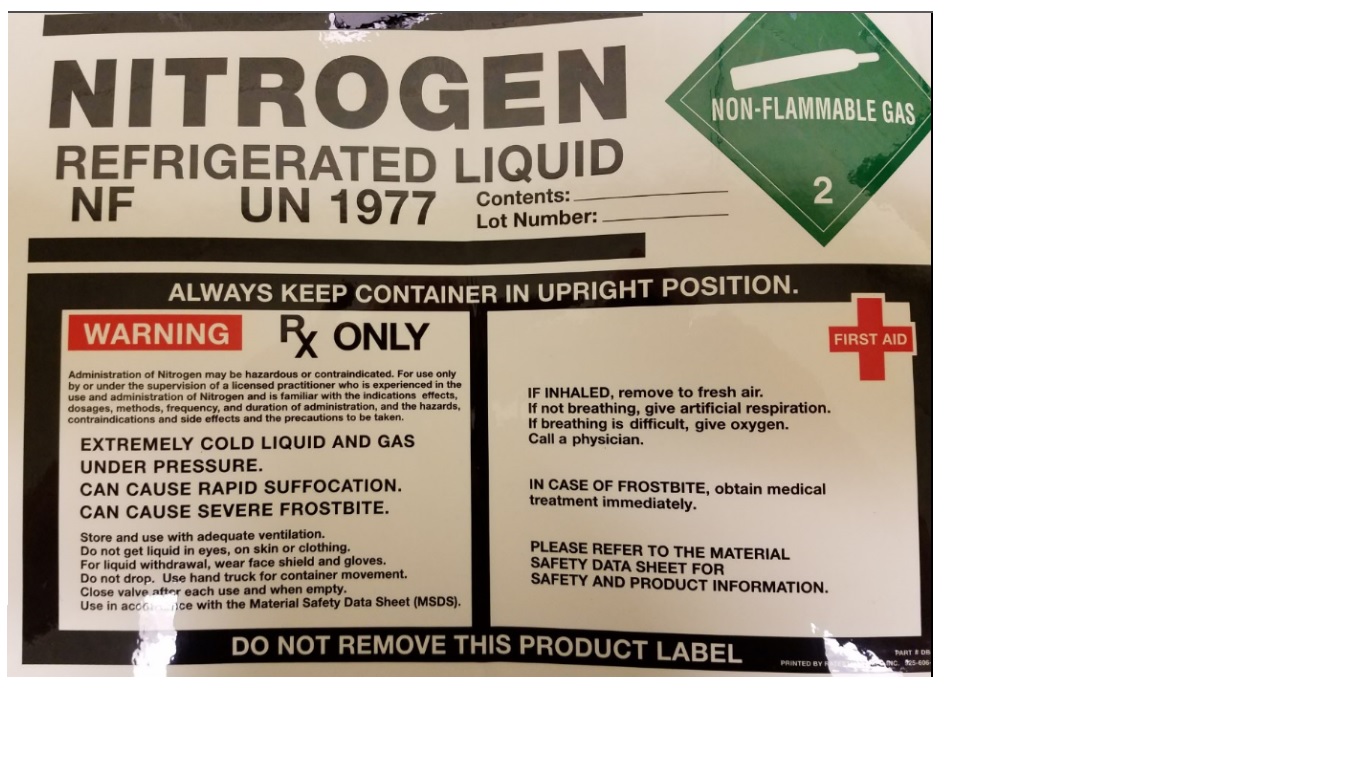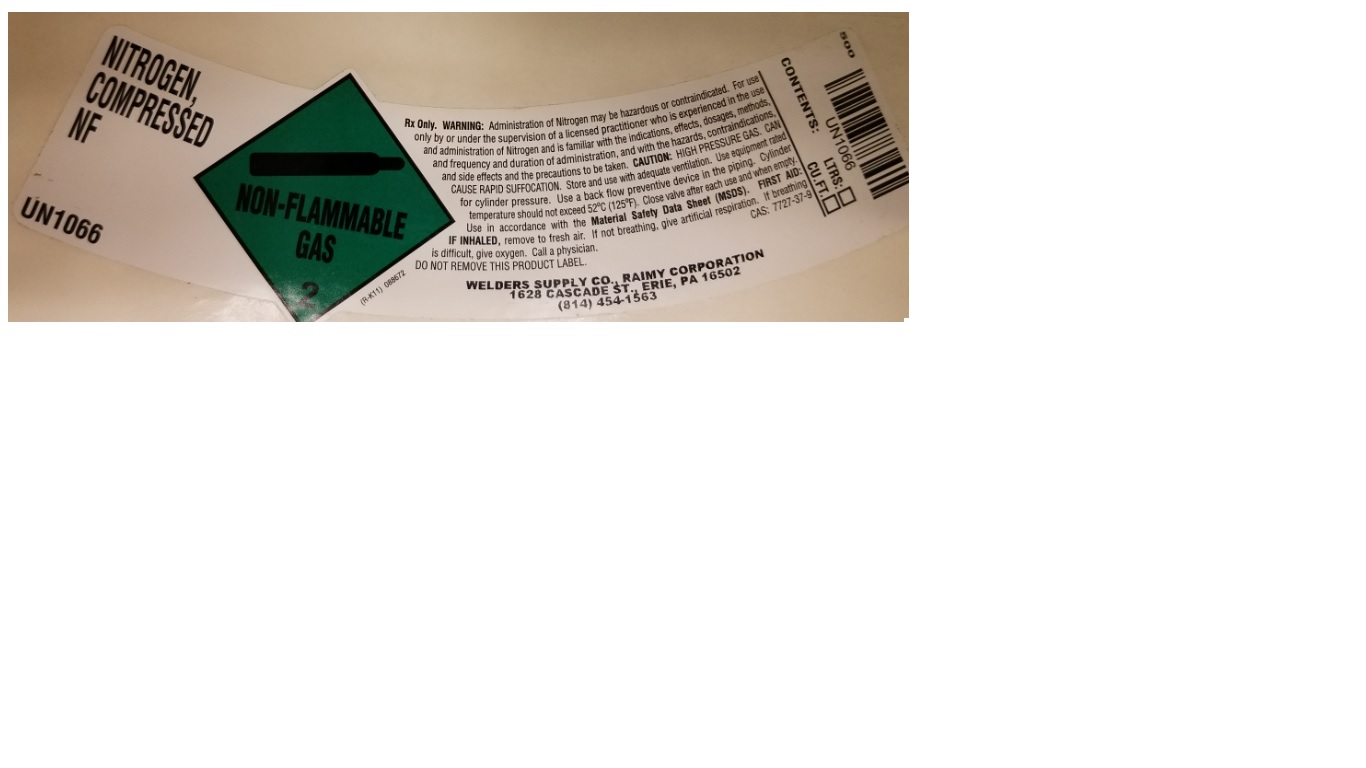 DRUG LABEL: Nitrogen
NDC: 10942-2011 | Form: GAS
Manufacturer: Raimy Corporation
Category: prescription | Type: HUMAN PRESCRIPTION DRUG LABEL
Date: 20251030

ACTIVE INGREDIENTS: NITROGEN 990 mL/1 L

Nitrogen - 2011

PACKAGE LABEL

NITROGEN

REFRIGERATED LIQUID NF

UN1977

ALWAYS KEEP CONTAINER IN UPRIGHT POSITION

WARNING RX ONLY

Administration of Nitrogen may be hazardous or contraindicated. For use only by or under the supervision of a licensed practitioner who is experienced in the use and administration of Nitrogen and is familiar with the indications effects, dosages, methods, frequency, and duration of administration, and the hazards, contraindications and side effects and the precautions to be taken.

EXTREMELY COLD LIQUID AND GAS UNDER PRESSURE.

CAN CAUSE RAPID SUFFOCATION.

CAN CAUSE SEVERE FROSTBITE.

Store and use with adequate ventilation.

Do not get liquid in eyes, on skin or clothing.

For liquid withdrawal, wear face shield and gloves.

Do not drop. Use hand truck for container movement.

Close valve after each use and when empty.

Use in accordance with the Material Safety Data Sheet (MSDS).

FIRST AID

IF INHALED, remove to fresh air.

If not breathing, give artificial respiration. If breathing is difficult, give oxygen.

Call a physician.

IN CASE OF FROSTBITE, obtain medical treatment immediately.

PLEASE REFER TO THE MATERIAL SAFETY DATA SHEET FOR SAFETY AND PRODUCT INFORMATION.

PACKAGE LABEL

NITROGEN, COMPRESSED NF

UN1066

Rx Only. WARNING: Administration of Nitrogen may be hazardous or contraindicated. For use only by or under the supervision of a licensed practitioner who is experienced in the use and administration of Nitrogen and is familiar with the indications, effects, dosages, methods, and frequency and duration of administration, and with the hazards, contraindications, and side effects and the precautions to be taken. CAUTION: HIGH PRESSURE GAS, CAN CAUSE RAPID SUFFOCATION. Store and use with adequate ventilation. Use equipment rated for cylinder pressure. Use a back flow preventive device in the piping. Cylinder temperature should not exceed 52 C (125 F). Close valve after each use and when empty. Use in accordance with the Material Safety Data Sheet (MSDS). FIRST AID: IF INHALED, remove to fresh air. If not breathing, give artificial respiration. If breathing is difficult, give oxygen. Call a physician.

DO NOT REMOVE THIS PRODUCT LABEL. CAS: 7727-37-9

WELDERS SUPPLY CO., RAIMY CORPORATION

1628 CASCADE ST., ERIE, PA 16502

(814) 454-1563